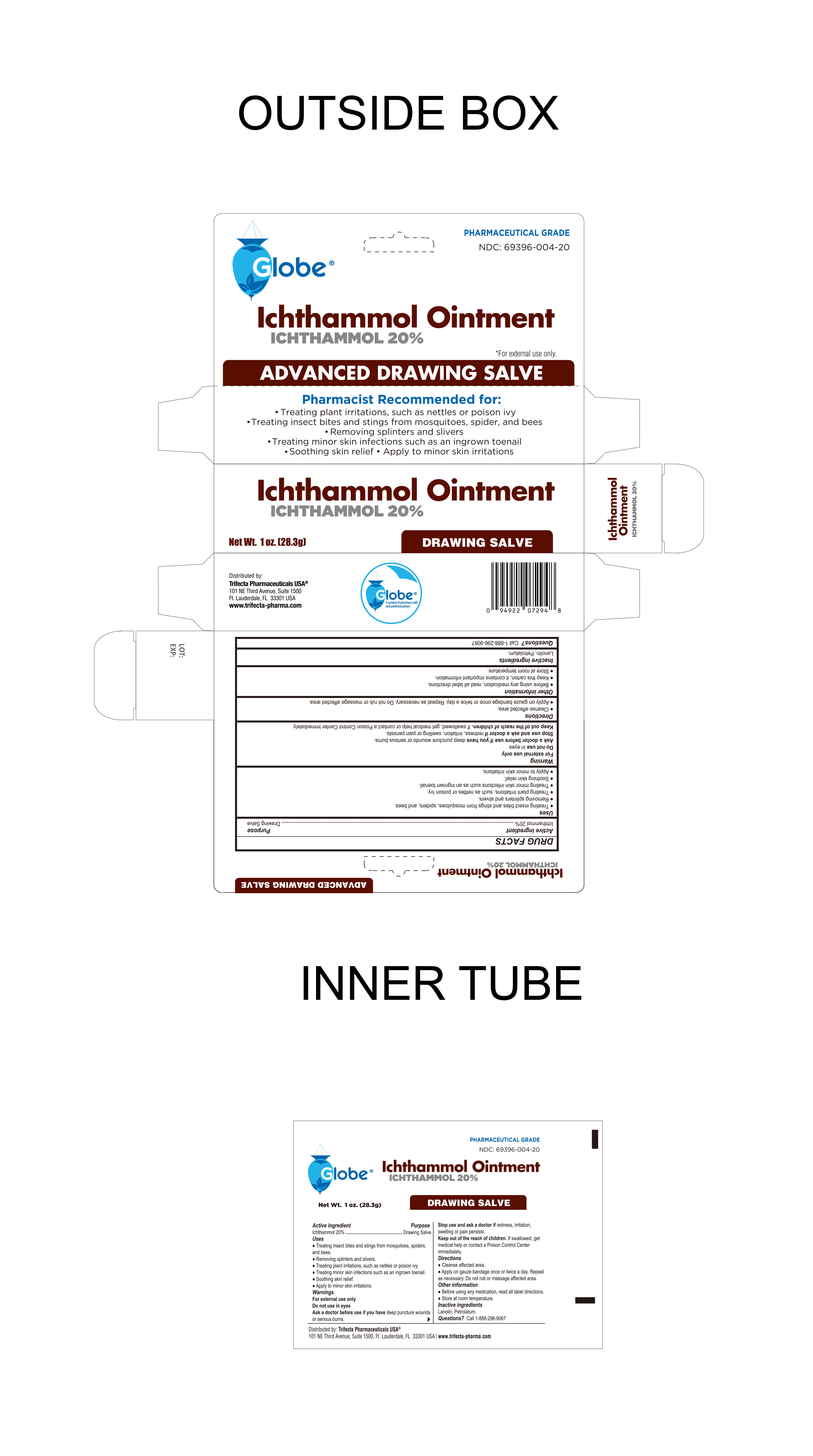 DRUG LABEL: Ichthammol 20%
NDC: 69396-004 | Form: OINTMENT
Manufacturer: TRIFECTA PHARMACEUTICALS USA LLC
Category: homeopathic | Type: HUMAN OTC DRUG LABEL
Date: 20241231

ACTIVE INGREDIENTS: ICHTHAMMOL 20 g/100 g
INACTIVE INGREDIENTS: PETROLATUM

Ichthammol Ointment 20%

Active ingredient

Ichthammol 20%

Purpose

Drawing Salve

Keep out of reach of children.

Suggested Use

• Treating insect bites and stings from mosquitoes, spider, and bees • Removing splinters and silvers • Treating plant irritations, such as nettles or poison ivy • Treating minor skin infections such as an ingrown toenail • Soothing skin relief • Apply to minor skin irritations

Warnings

• For external use only • Do not use in eyes • Ask a doctor before use if you have deep puncture wounds or serious burns • Stop use and ask doctor if redness, irritation, swelling or pain persists

If swallowed, get medical help or contact a Poison Control Center immediately.

Before using any medication, read all label directions.

Keep this carton, it contains important information.

Directions

Cleanse affected area. Apply on gauze bandage once or twice a day. Repeat as necessary. Do not rub or massage affected area.

Inactive Ingredients

Lanolin, Petrolatum

Distributed by:

Trifecta Pharmaceuticals USATM

101 NE Third Avenue, Suite 1500

Ft. Lauderdale, FL 33301 USA

1-888-296-9067